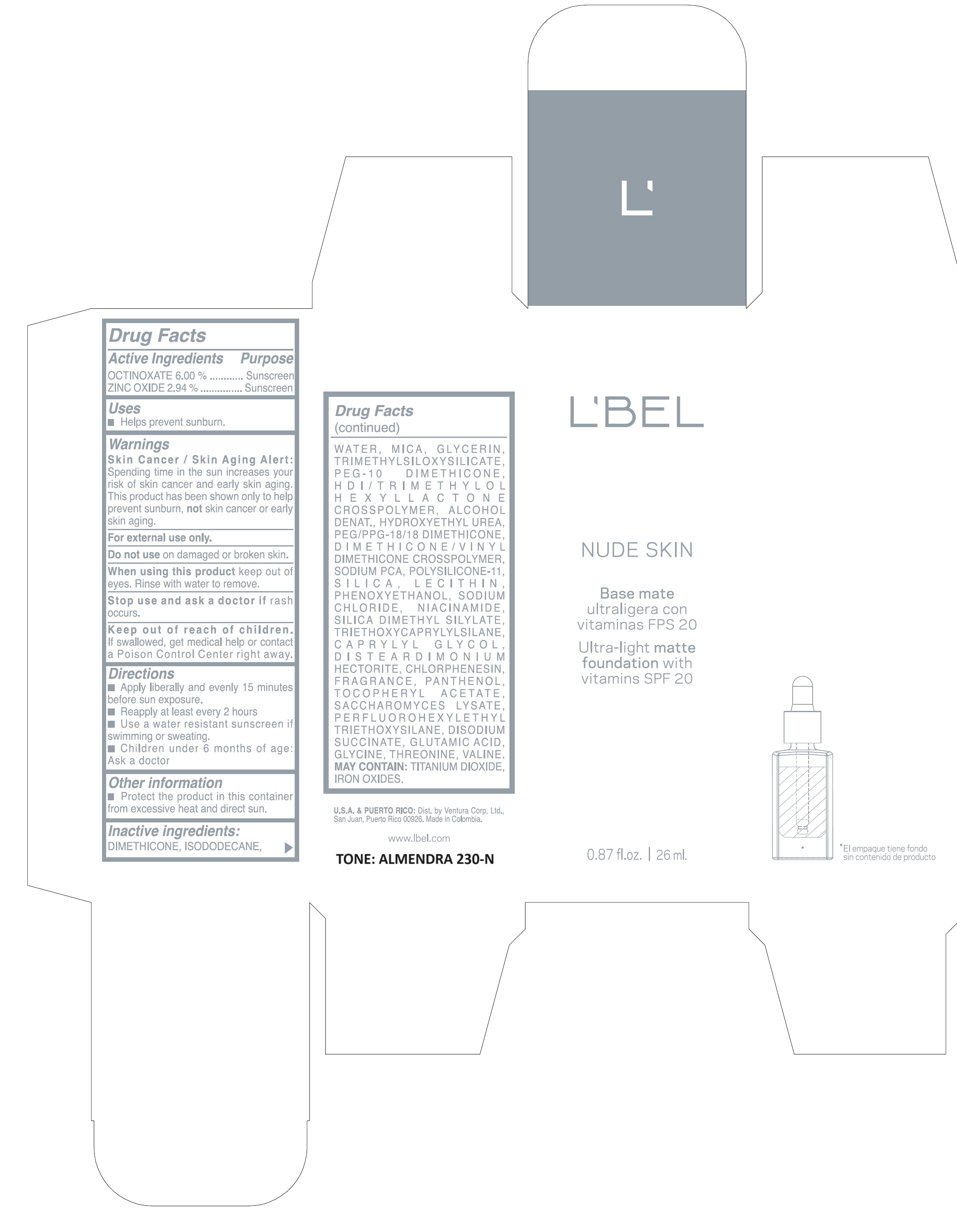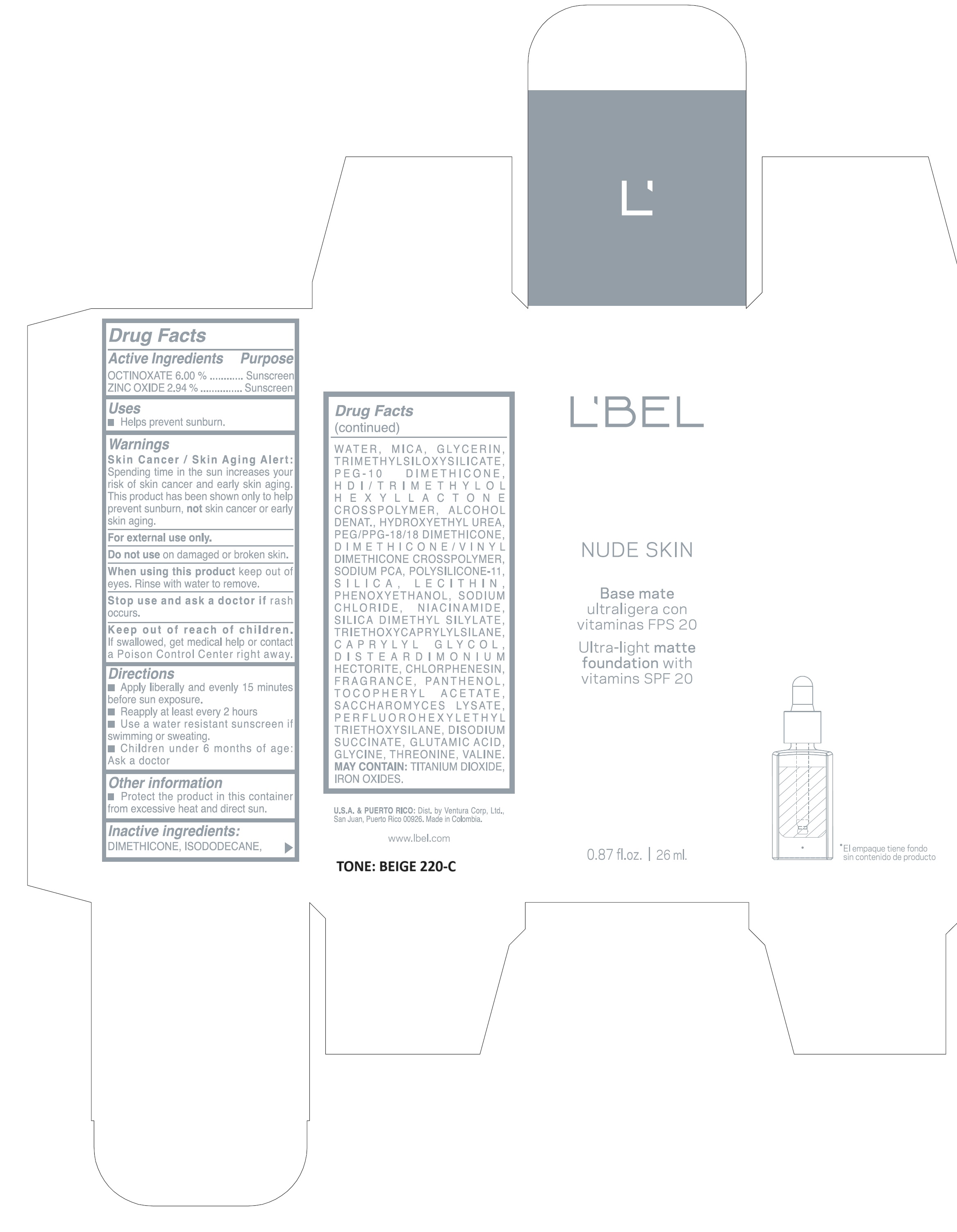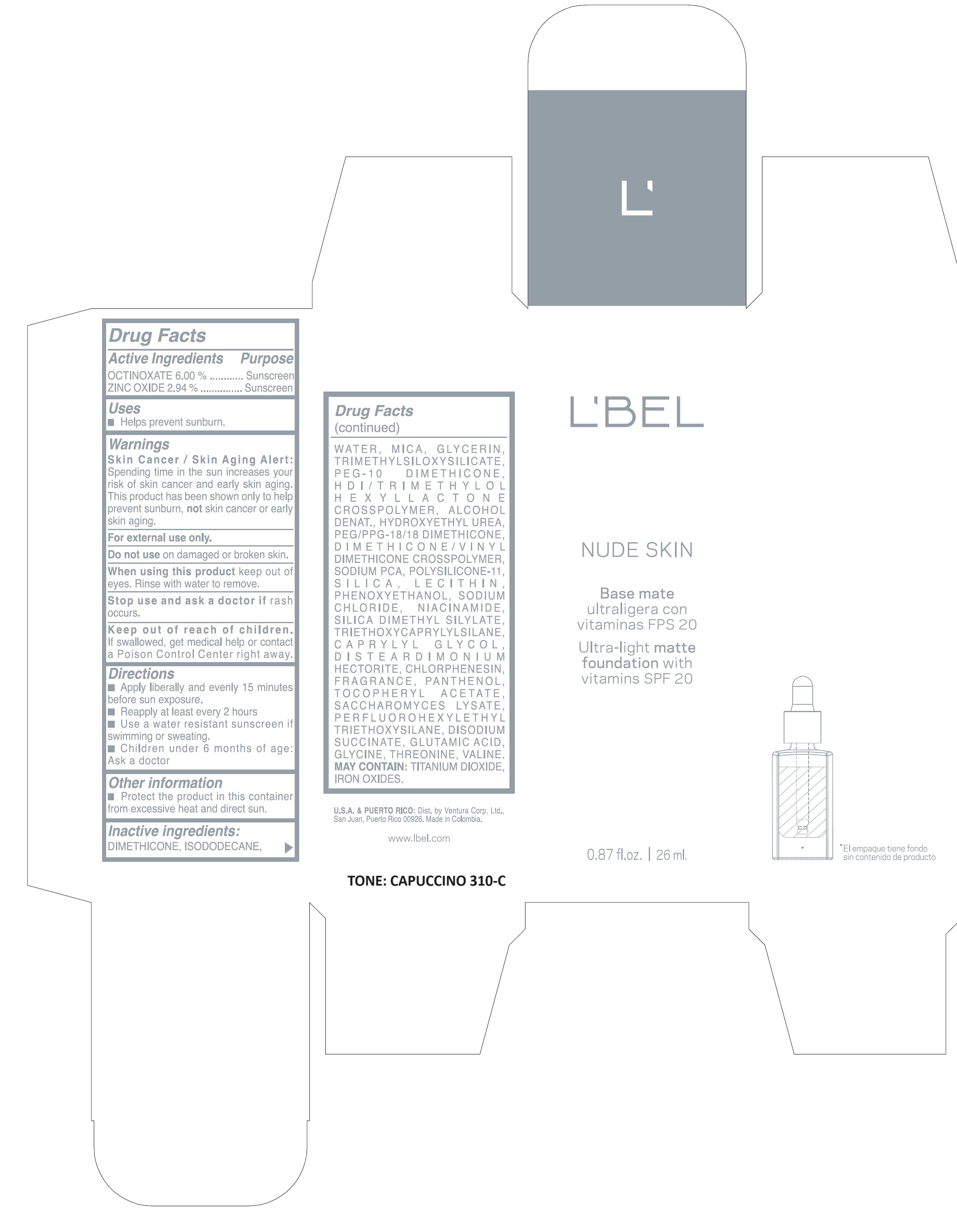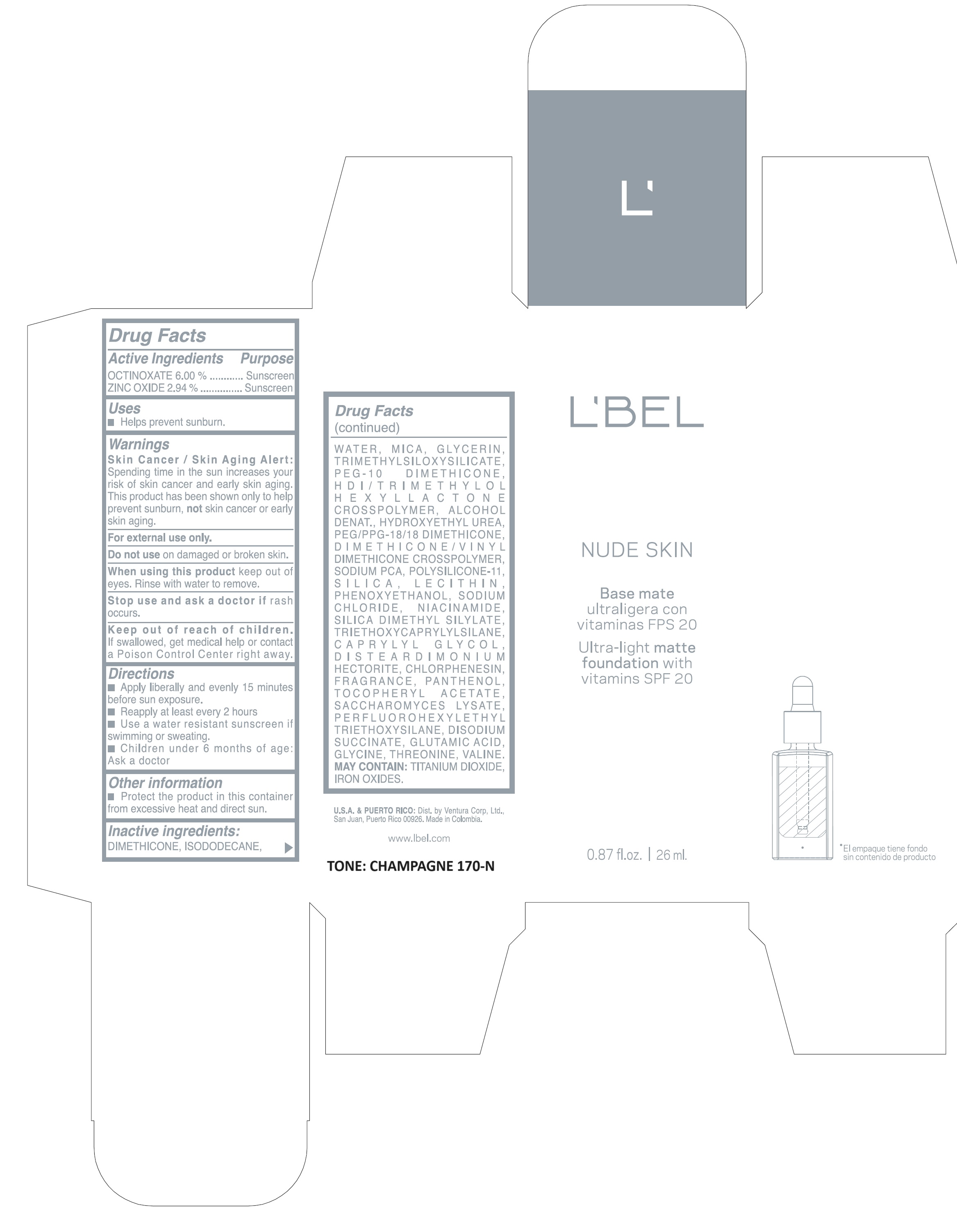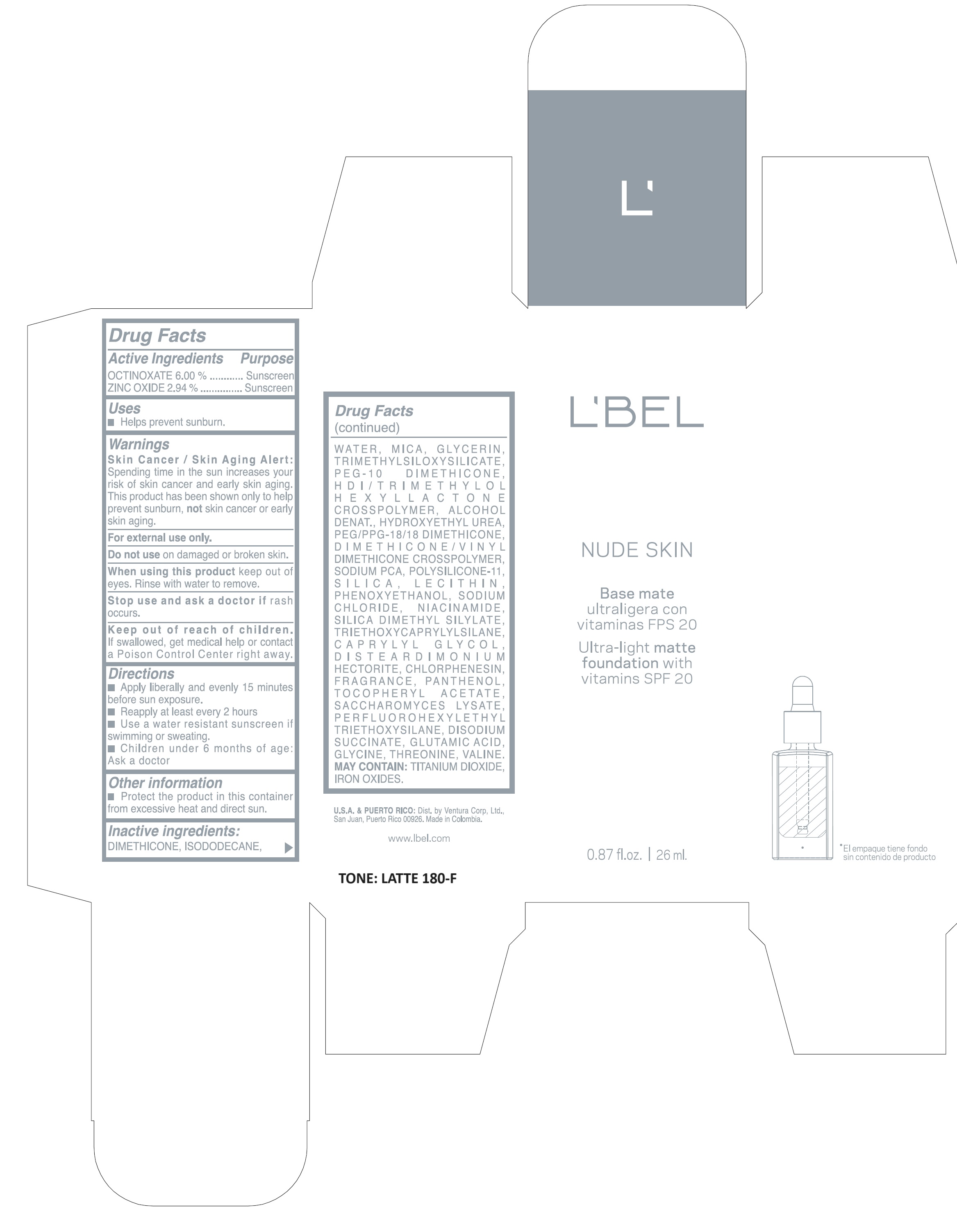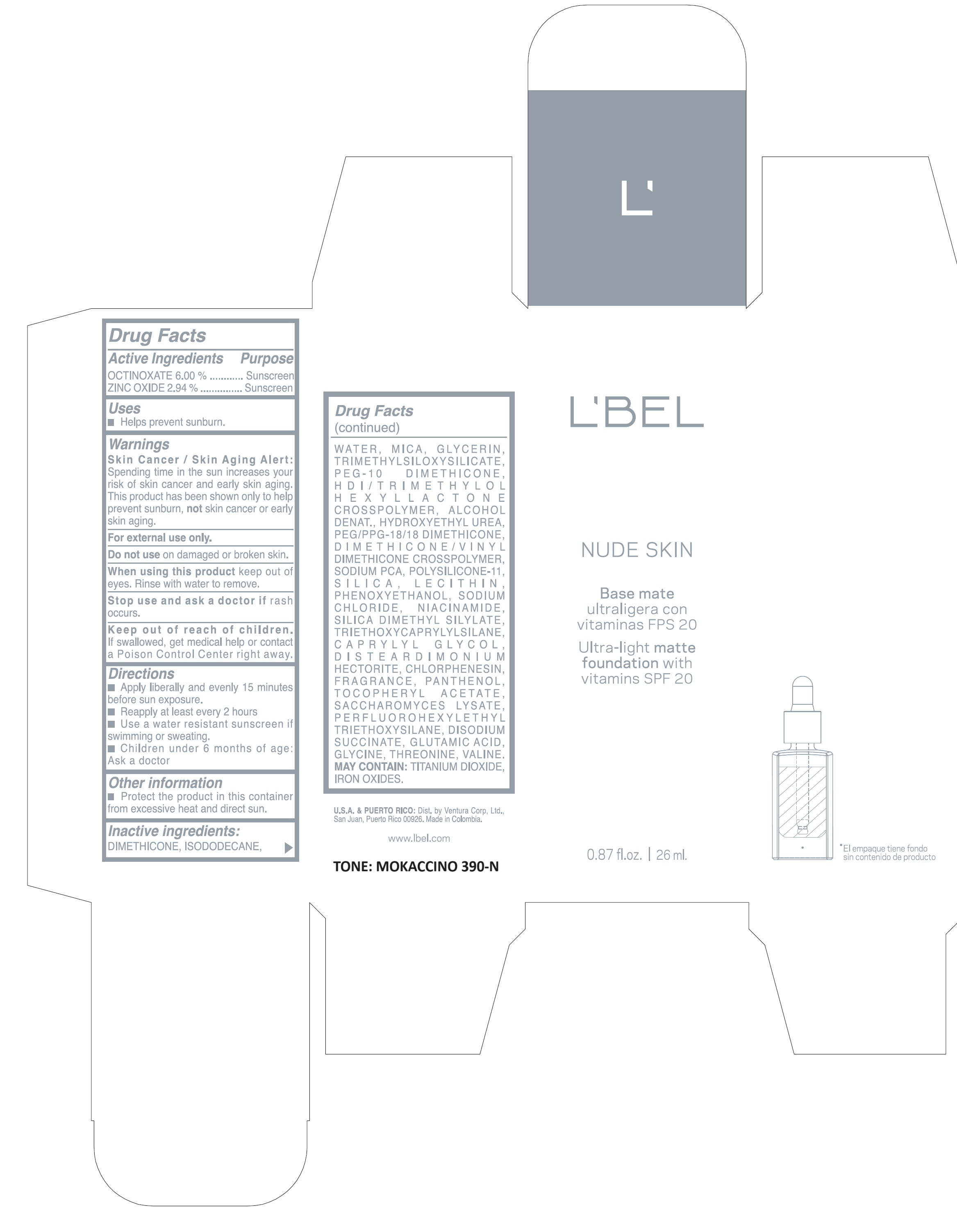 DRUG LABEL: LBEL NUDE SKIN ULTRA LIGHT MATTE FOUNDATION WITH VITAMINS SPF 20 LATTE 180-F
NDC: 14141-021 | Form: EMULSION
Manufacturer: Bel Star S.A.
Category: otc | Type: HUMAN OTC DRUG LABEL
Date: 20250619

ACTIVE INGREDIENTS: OCTINOXATE 60 mg/1 mL; ZINC OXIDE 29.4 mg/1 mL
INACTIVE INGREDIENTS: HYDROXYETHYL UREA; .ALPHA.-TOCOPHEROL ACETATE; SACCHAROMYCES LYSATE; THREONINE; WATER; LECITHIN, SOYBEAN; PANTHENOL; VALINE; DIMETHICONE; GLYCERIN; PEG/PPG-18/18 DIMETHICONE; HEXAMETHYLENE DIISOCYANATE/TRIMETHYLOL HEXYLLACTONE CROSSPOLYMER; ALCOHOL; SODIUM SUCCINATE ANHYDROUS; GLUTAMIC ACID; GLYCINE; CHLORPHENESIN; SILICON DIOXIDE; SILICA DIMETHYL SILYLATE; SODIUM CHLORIDE; TITANIUM DIOXIDE; FERRIC OXIDE YELLOW; FERROSOFERRIC OXIDE; TRIMETHYLSILOXYSILICATE (M/Q 0.6-0.8); FERRIC OXIDE RED; NIACINAMIDE; PEG-10 DIMETHICONE (600 CST); PHENOXYETHANOL; DISTEARDIMONIUM HECTORITE; TRIETHOXYCAPRYLYLSILANE; CAPRYLYL GLYCOL; ISODODECANE; MICA; SODIUM PYRROLIDONE CARBOXYLATE; DIMETHICONE/VINYL DIMETHICONE CROSSPOLYMER (SOFT PARTICLE)

LBEL NUDE SKIN ULTRA-LIGHT MATTE FOUNDATION WITH VITAMINS SPF 20

Active Ingredients

OCTINOXATE 6.00%

ZINC OXIDE 2.94%

Purpose

Sunscreen

Uses

- Helps prevent sunburn.

Warnings

- Skin Cancer/Skin Aging Alert: Spending time in the sun increases your risk of skin cancer and early skin aging. This product has been shown only to help prevent sunburn, not skin cancer or early skin aging.
- For external use only.

Do not use

on damaged or broken skin.

When using this product

keep out eyes. Rinse with water to remove.

Stop use and ask a doctor

if rash occurs.

Keep out of reach of children.

If swallowed, get medical help or contact a Poison Control Center right away.

Directions

- Apply liberally and evenly 15 minutes before sun exposure.
- Reapply at least every 2 hours.
- Use a water resistant sunscreen if swimming or sweating.
- Children under 6 months of age: Ask a doctor.

Other information

- Protect the product in this container from excessive heat and direct sun.

Inactive ingredients

DIMETHICONE, ISODODECANE, WATER, MICA, GLYCERIN, TRIMETHYLSILOXYSILICATE, PEG-10 DIMETHICONE, HDI/TRIMETHYLOL HEXYLLACTONE CROSSPOLYMER, ALCOHOL DENAT., HYDROXYETHYL UREA, PEG/PPG-18/18 DIMETHICONE, DIMETHICONE/VINYL DIMETHICONE CROSSPOLYMER, SODIUM PCA, POLYSILICONE-11, SILICA, LECITHIN, PHENOXYETHANOL, SODIUM CHLORIDE, NIACINAMIDE, SILICA DIMETHYL SILYLATE, TRIETHOXYCAPRYLYLSILANE, CAPRYLYL GLYCOL, DISTEARDIMONIUM HECTORITE, CHLORPHENESIN, FRAGRANCE, PANTHENOL, TOCOPHERYL ACETATE, SACCHAROMYCES LYSATE, PERFLUOROHEXYLETHYL TRIETHOXYSILANE, DISODIUM SUCCINATE, GLUTAMIC ACID, GLYCINE, THREONINE, VALINE. MAY CONTAIN: TITANIUM DIOXIDE, IRON OXIDES.

Company Information

U.S.A.& PUERTO RICO: Dist. BY Ventura Corp. Ltd., San Juan, Puerto Rico 00926.

Made in Colombia.

www.lbel.com